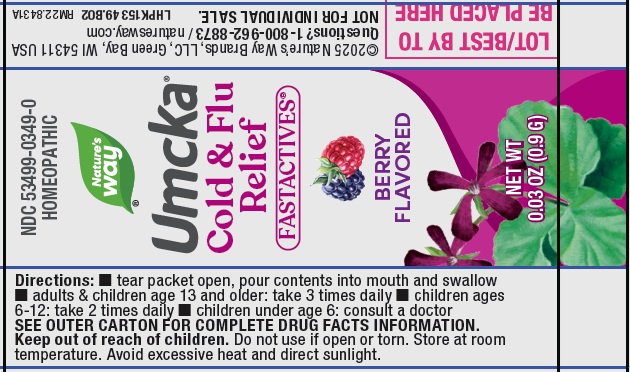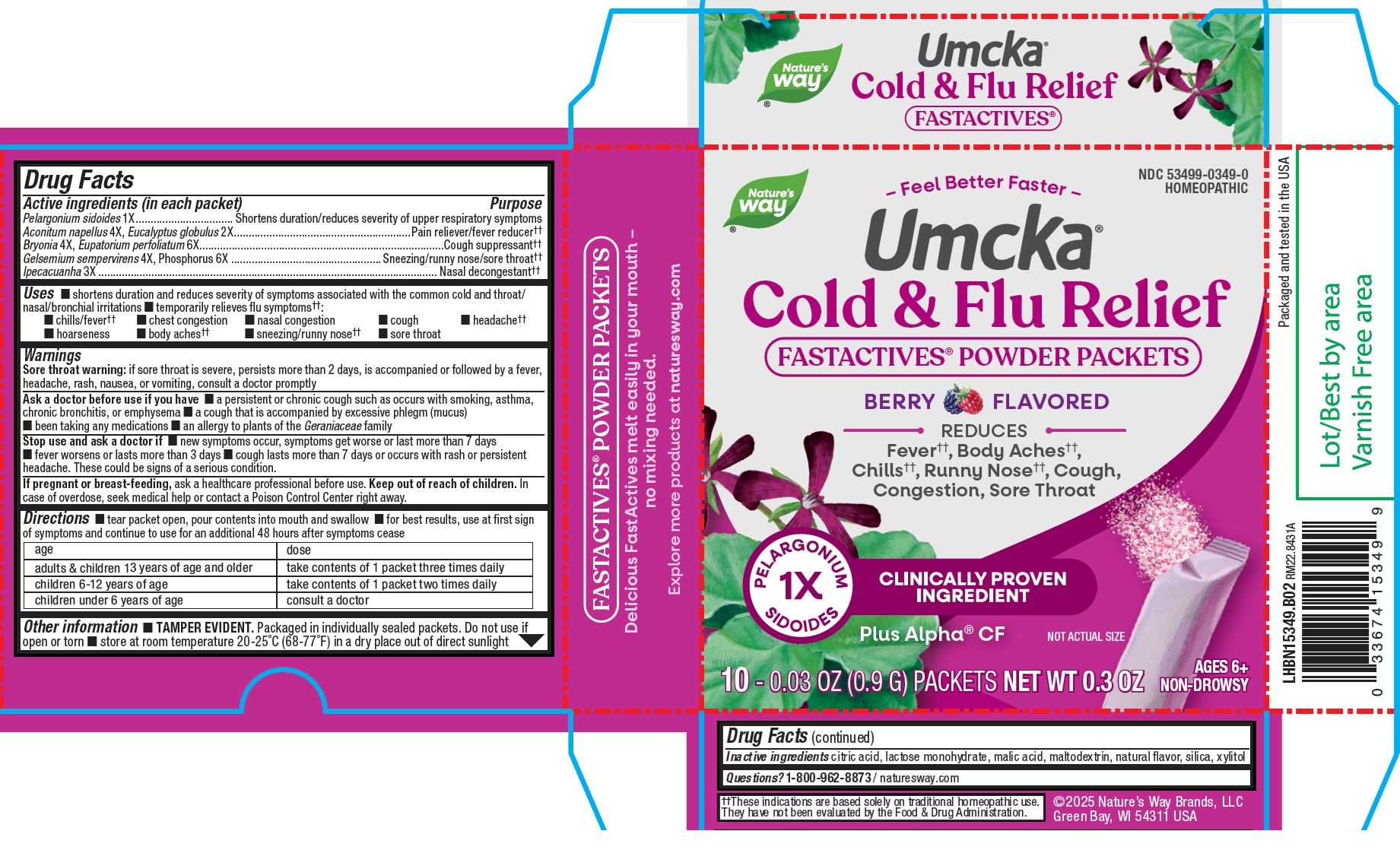 DRUG LABEL: Natures Way Cold Flu Relief Fastactives Berry Flavored
NDC: 80228-0349 | Form: POWDER
Manufacturer: Universal Synergetics, Inc
Category: homeopathic | Type: HUMAN OTC DRUG LABEL
Date: 20250814

ACTIVE INGREDIENTS: PELARGONIUM SIDOIDES WHOLE 1 [hp_X]/1 g; ACONITUM NAPELLUS WHOLE 4 [hp_X]/1 g; EUCALYPTUS GLOBULUS LEAF 2 [hp_X]/1 g; BRYONIA ALBA ROOT 4 [hp_X]/1 g; EUPATORIUM PERFOLIATUM FLOWERING TOP 6 [hp_X]/1 g; GELSEMIUM SEMPERVIRENS ROOT 4 [hp_X]/1 g; PHOSPHORUS 6 [hp_X]/1 g; IPECAC 3 [hp_X]/1 g
INACTIVE INGREDIENTS: CITRIC ACID MONOHYDRATE; LACTOSE MONOHYDRATE; MALIC ACID; MALTODEXTRIN; SILICON DIOXIDE; XYLITOL

Nature’s Way Cold Flu Relief Fastactives, Berry Flavored

Active ingredients (in each packet)

Pelargonium sidoides 1X

Aconitum napellus 4X, Eucalyptus globulus 2X

Bryonia 4X, Eupatorium perfoliatum 6X

Gelsemium sempervirens 4X, Phosphorus 6X

Ipecacuanha 3X

Purpose

Shortens duration/reduces severity of upper respiratory symptoms

Pain reliever/fever reducer

Cough suppressant

Sneezing/runny nose/sore throat

Nasal decongestant

Uses

- shortens duration and reduces severity of symptoms associated with the common cold and throat/ nasal/bronchial irritations
- temporarily relieves flu symptoms
- chills/fever
- chest congestion
- nasal congestion
- cough
- headache
- hoarseness
- body aches
- sneezing/runny nose
- sore throat

Warnings

Sore throat warning:if sore throat is severe, persists more than 2 days, is accompanied or followed by a fever, headache, rash, nausea, or vomiting, consult a doctor promptly

Ask a doctor before use if you have

- a persistent or chronic cough such as occurs with smoking, asthma, chronic bronchitis, or emphysema
- a cough that is accompanied by excessive phlegm (mucus)
- been taking any medications
- an allergy to plants of the Geraniaceaefamily

Stop use and ask a doctor if

- new symptoms occur, symptoms get worse or last more than 7 days
- fever worsens or lasts more than 3 days
- cough lasts more than 7 days or occurs with rash or persistent headache. These could be signs of a serious condition.

If pregnant or breast-feeding,

ask a healthcare professional before use.

Keep out of reach of children.

In case of overdose, seek medical help or contact a Poison Control Center right away.

Directions

- tear packet open, pour contents into mouth and swallow
- for best results, use at first sign of symptoms and continue to use for an additional 48 hours after symptoms cease

age | Dose
adults & children 13 years of age and older | take contents of 1 packet three times daily
children 6 -12 years of age | take contents of 1 packet two times daily
children under 6 years of age | consult a doctor

Other information

- TAMPER EVIDENT.Packaged in individually sealed packets. Do not use if open or torn
- store at room temperature 20-25°C (68-77°F) in a dry place out of direct sunlight

Inactive ingredients

citric acid, lactose monohydrate, malic acid, maltodextrin, natural flavor, silica, xylitol

Questions?

1-800-962-8873/ naturesway.com